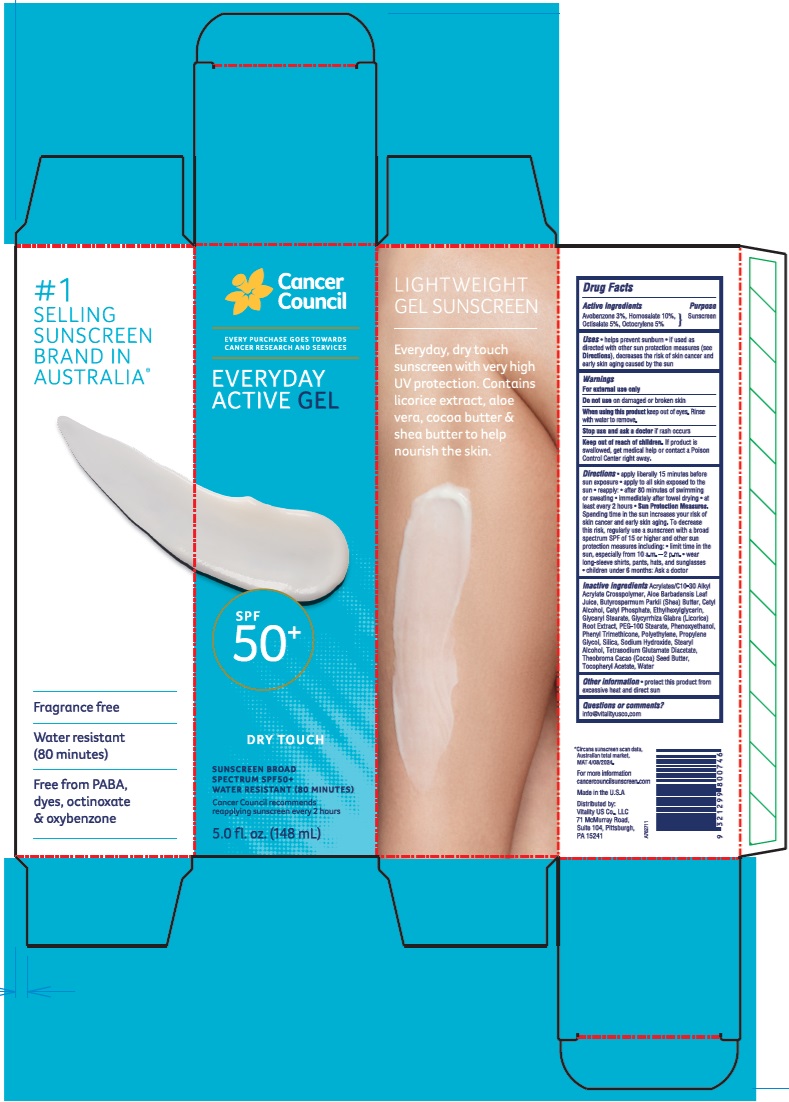 DRUG LABEL: Cancer Council Everyday Active SPF50 Plus
NDC: 84258-004 | Form: GEL
Manufacturer: Vitality US Co.
Category: otc | Type: HUMAN OTC DRUG LABEL
Date: 20240416

ACTIVE INGREDIENTS: HOMOSALATE 100 mg/1 mL; OCTOCRYLENE 50 mg/1 mL; OCTISALATE 50 mg/1 mL; AVOBENZONE 30 mg/1 mL
INACTIVE INGREDIENTS: .ALPHA.-TOCOPHEROL ACETATE; ACRYLATES/C10-30 ALKYL ACRYLATE CROSSPOLYMER (60000 MPA.S); SHEA BUTTER; WATER; CETYL ALCOHOL; ALOE VERA LEAF; CETYL PHOSPHATE; ETHYLHEXYLGLYCERIN; GLYCERYL MONOSTEARATE; GLYCYRRHIZA GLABRA; PEG-100 STEARATE; PHENOXYETHANOL; PHENYL TRIMETHICONE; HIGH DENSITY POLYETHYLENE; PROPYLENE GLYCOL; SILICON DIOXIDE; SODIUM HYDROXIDE; STEARYL ALCOHOL; TETRASODIUM GLUTAMATE DIACETATE; COCOA BUTTER

Cancer Council Everyday Active Gel SPF50 Plus

Active Ingredients

Avobenzone 3%

Homosalate 10%

Octisalate 5%

Octocrylene 5%

Purpose

Sunscreen

Uses

- helps prevent sunburn
- if used as directed with other sun protection measures (see Directions), decreases the risk of skin cancer and early skin aging caused by the sun

Warnings

For external use only

Do not use

on damaged or broken skin

When using this product

keep out of eyes. Rinse with water to remove.

Stop use and ask a doctor

if rash occurs

Keep out of reach of children.

If product is swallowed, get medical help or contact a Poison Control Center right away.

Directions

- apply liberally 15 minutes before sun exposure
- apply to all skin exposed to the sun
- reapply:
- after 80 minutes of swimming or sweating
- immediately after towel drying
- at least every 2 hours
- Sun Protection Measures. Spending time in the sun increases your risk of skin cancer and early skin aging. To decrease this risk, regularly use a sunscreen with a broad spectrum SPF of 15 or higher and other sun protection measures including:
- limit time in the sun, especially from 10 a.m. - 2 p.m.
- wear long-sleeve shirts, pants, hats, and sunglasses
- children under 6 months: Ask a doctor

Inactive ingredients

Acrylates/C10-30 Alkyl Acrylate Crosspolymer, Aloe Barbadensis Leaf Juice, Butyrospermum Parkii (Shea) Butter, Cetyl Alcohol, Cetyl Phosphate, Ethylhexylglycerin, Glyceryl Stearate, Glycyrrhiza Glabra (Licorice) Root Extract, PEG-100 Stearate, Phenoxyethanol, Phenyl Trimethicone, Polyethylene, Propylene Glycol, Silica, Sodium Hydroxide, Stearyl Alcohol, Tetrasodium Glutamate Diacetate, Theobroma Cacao (Cocoa) Seed Butter, Tocopheryl Acetate, Water

Other information

- protect this product from excessive heat and direct sun

Questions or comments?

info@vitalityusco.com